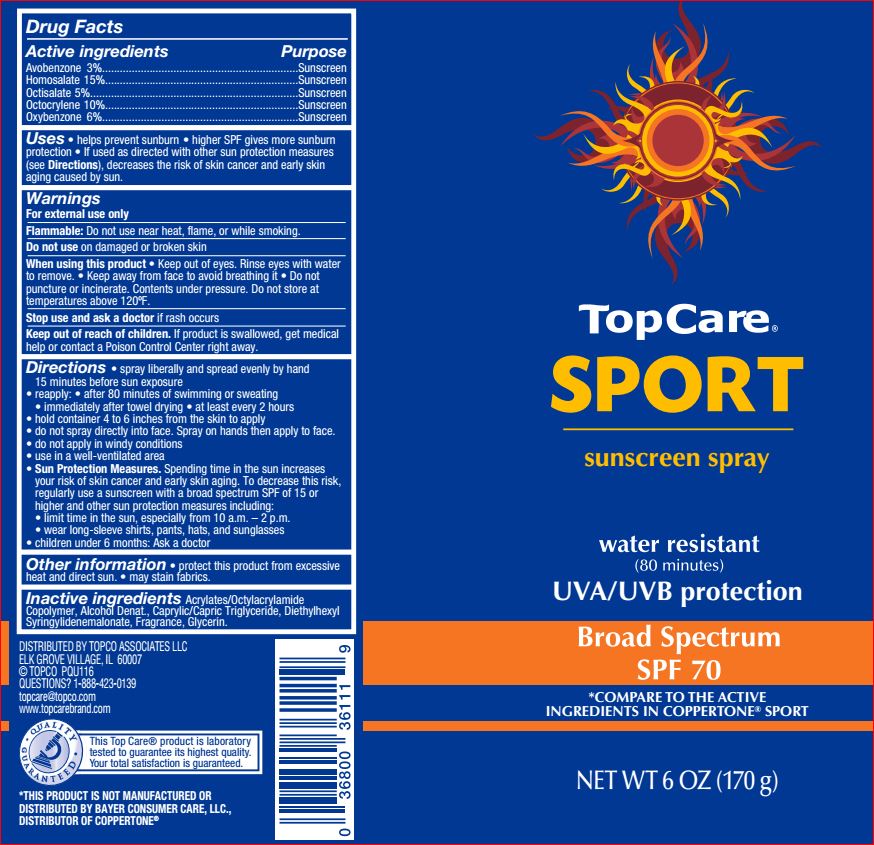 DRUG LABEL: Sport Sunscreen SPF 70
NDC: 36800-728 | Form: SPRAY
Manufacturer: TopCare
Category: otc | Type: HUMAN OTC DRUG LABEL
Date: 20180717

ACTIVE INGREDIENTS: Avobenzone 3 g/100 g; Homosalate 15 g/100 g; Octisalate 5 g/100 g; Octocrylene 10 g/100 g; Oxybenzone 6 g/100 g
INACTIVE INGREDIENTS: ALCOHOL; MEDIUM-CHAIN TRIGLYCERIDES; Diethylhexyl Syringylidenemalonate; Glycerin

Drug Facts

Active ingredients Purpose
Avobenzone 3%..................................................................Sunscreen
Homosalate 15%.................................................................Sunscreen
Octisalate 5%......................................................................Sunscreen
Octocrylene 10%.................................................................Sunscreen
Oxybenzone 6%..................................................................Sunscreen

INDICATIONS AND USAGE

Uses • helps prevent sunburn • higher SPF gives more sunburn
protection • If used as directed with other sun protection measures
(see Directions), decreases the risk of skin cancer and early skin
aging caused by sun.

Warnings
For external use only
Flammable: Do not use near heat, flame, or while smoking.
Do not use on damaged or broken skin
When using this product • Keep out of eyes. Rinse eyes with water
to remove. • Keep away from face to avoid breathing it • Do not
puncture or incinerate. Contents under pressure. Do not store at
temperatures above 120ºF.
Stop use and ask a doctor if rash occurs

Keep out of reach of children. If product is swallowed, get medical help or contact a Poison Control Center right away

Directions

• spray liberally and spread evenly by hand
15 minutes before sun exposure
• reapply: • after 80 minutes of swimming or sweating
• immediately after towel drying • at least every 2 hours
• hold container 4 to 6 inches from the skin to apply
• do not spray directly into face. Spray on hands then apply to face.
• do not apply in windy conditions
• use in a well-ventilated area
• Sun Protection Measures. Spending time in the sun increases
your risk of skin cancer and early skin aging. To decrease this risk,
regularly use a sunscreen with a broad spectrum SPF of 15 or
higher and other sun protection measures including:
• limit time in the sun, especially from 10 a.m. – 2 p.m.
• wear long-sleeve shirts, pants, hats, and sunglasses
• children under 6 months: Ask a doctor

Other information • protect this product from excessive heat and direct sun. • may stain fabrics.

Inactive Ingredients:
Acrylates/Octylacrylamide Copolymer
Alcohol Denat.
Caprylic/Capric Triglyceride
Diethylhexyl Syringylidenemalonate
Fragrance
Glycerin